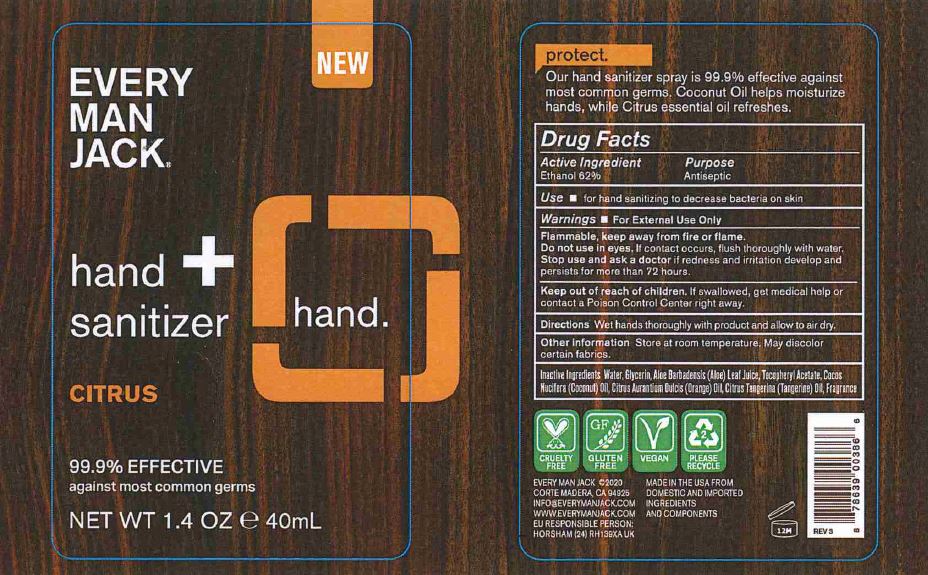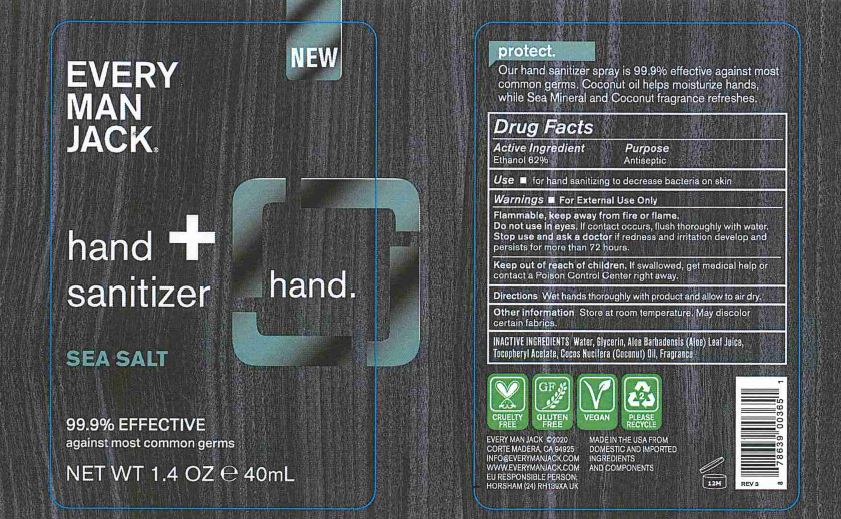 DRUG LABEL: EVERY MAN JACK - HAND SANITIZER
NDC: 57934-5015 | Form: SPRAY
Manufacturer: EVERY MAN JACK
Category: otc | Type: HUMAN OTC DRUG LABEL
Date: 20211227

ACTIVE INGREDIENTS: ALCOHOL 62 mL/100 mL
INACTIVE INGREDIENTS: WATER; GLYCERIN; .ALPHA.-TOCOPHEROL ACETATE; COCONUT OIL; ORANGE OIL; ALOE VERA LEAF; TANGERINE

EVERY MAN JACK - HAND SANITIZER, SPRAY (62% ETHANOL), 57934-5015

ACTIVE INGREDIENT

ETHANOL 62%

PURPOSE

ANTISEPTIC

USES

FOR HAND SANITIZING TO DECREASE BACTERIA ON SKIN.

WARNINGS

- FOR EXTERNAL USE ONLY.

FLAMMABLE, KEEP AWAY FROM FIRE OR FLAME.

DO NOT USE IN EYES. IF CONTACT OCCURS, FLUSH THOROUGHLY WITH WATER.

STOP USE AND ASK A DOCTOR IF REDNESS AND IRRITATION DEVELOP AND PERSISTS FOR MORE THAN 72 HOURS.

KEEP OUT OF REACH OF CHILDREN. IF SWALLOWED, GET MEDICAL HELP OR CONTACT A POISON CONTROL CENTER RIGHT AWAY.

DIRECTIONS

WET HANDS THOROUGHLY WITH PRODUCT AND ALLOW TO AIR DRY.

OTHER INFORMATION

STORE AT ROOM TEMPERATURE. MAY DISCOLOR CERTAIN FABRICS.

INACTIVE INGREDIENTS

CITRUS: WATER, GLYCERIN, ALOE BARBADENSIS (ALOE) LEAF JUICE, TOCOPHERYL ACETATE, COCOS NUCIFERA (COCONUT) OIL, CITRUS AURANTIUM DULCIS (ORANGE) OIL, CITRUS TANGERINA (TANGERINE) OIL, FRAGRANCE

SEA SALT: WATER, GLYCERIN, ALOE BARBADENSIS (ALOE) LEAF JUICE, TOCOPHERYL ACETATE, COCOS NUCIFERA (COCONUT) OIL, FRAGRANCE